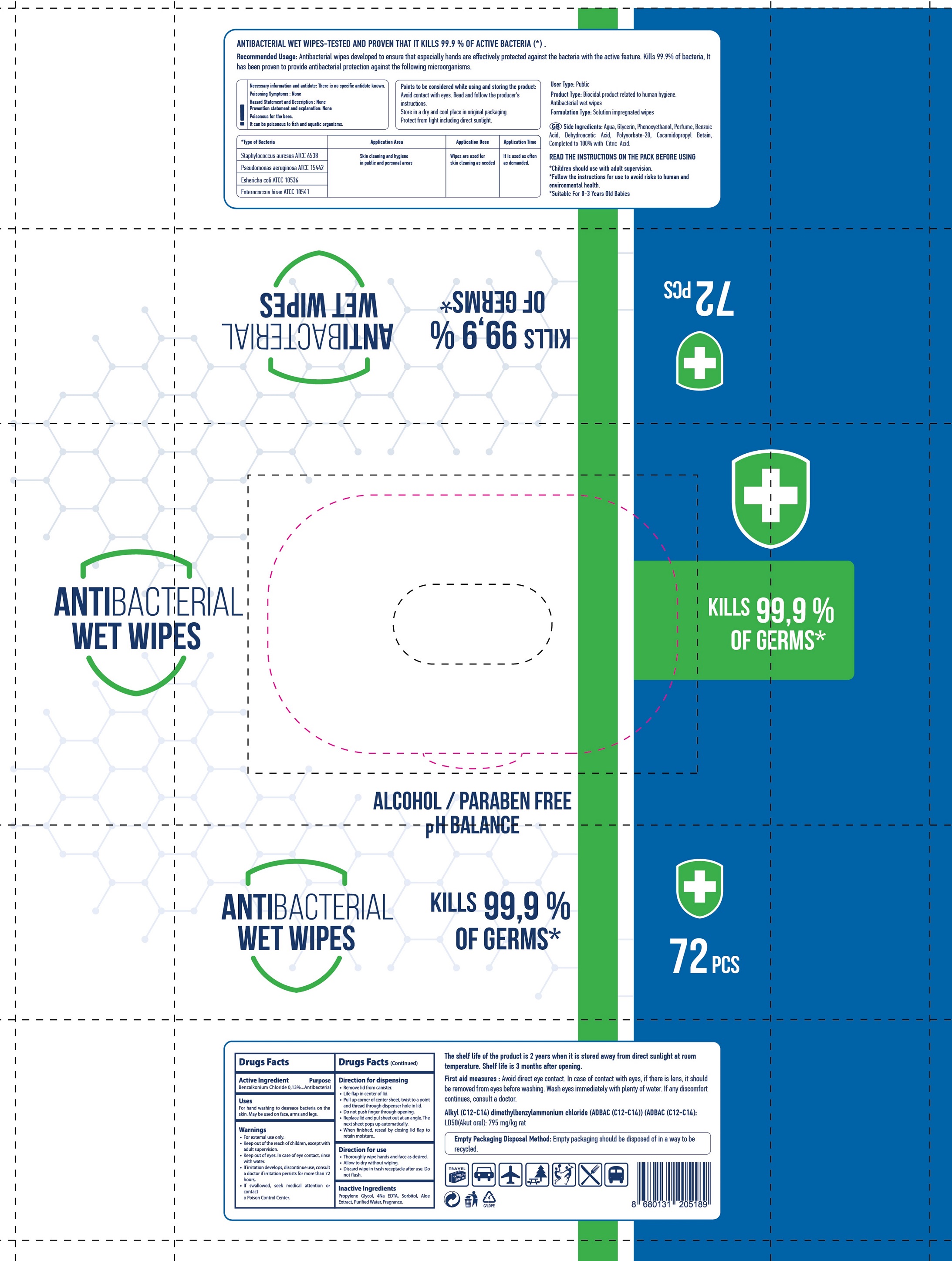 DRUG LABEL: GIGGLES ANTIBACTERIAL WET WIPES
NDC: 80088-001 | Form: CLOTH
Manufacturer: SEVINCLER SAGLIK URUNLERI SANAYI VE TICARET ANONIM SIRKETI
Category: otc | Type: HUMAN OTC DRUG LABEL
Date: 20200827

ACTIVE INGREDIENTS: BENZALKONIUM CHLORIDE 1.3 mg/1 g
INACTIVE INGREDIENTS: PROPYLENE GLYCOL; SORBITOL; ALOE VERA LEAF; WATER

GIGGLES ANTIBACTERIAL WET WIPES

Active Ingredient

Benzalkonium Chloride 0.13%

Purpose

Antibacterial

Uses

For hand washing to decrease bacteria on the skin. May be used on face, arms and legs.

Warnings

- For external use only.

KEEP OUT OF REACH OF CHILDREN

- Keep out of the reach of children, except with adult supervision.
- Keep out of eyes. In case of eye contact, rinse with water.
- If irritation develops, discontinue use, consult a doctor if irritation persists for more than 72 hours,
- If swallowed, seek medical attention or contact a Poison Control Center.

Direction for dispensing

- Remove lid from canister.
- Life flap in center of lid.
- Pull up corner of center sheet, twist to a point and thread through dispenser hole in lid.
- Do not push finger through opening.
- Replace lid and pul sheet out at an angle. The next sheet pops up automatically.
- When finished, reseal by closing lid flap to retain moisture.

Direction for use

- Thoroughly wipe hands and face as desired.
- Allow to dry without wiping.
- Discard wipe in trash receptacle after use. Do not flush.

Inactive Ingredients

Propylene Glycol, 4Na EDTA, Sorbitol, Aloe Extract, Purified Water, Fragrance.